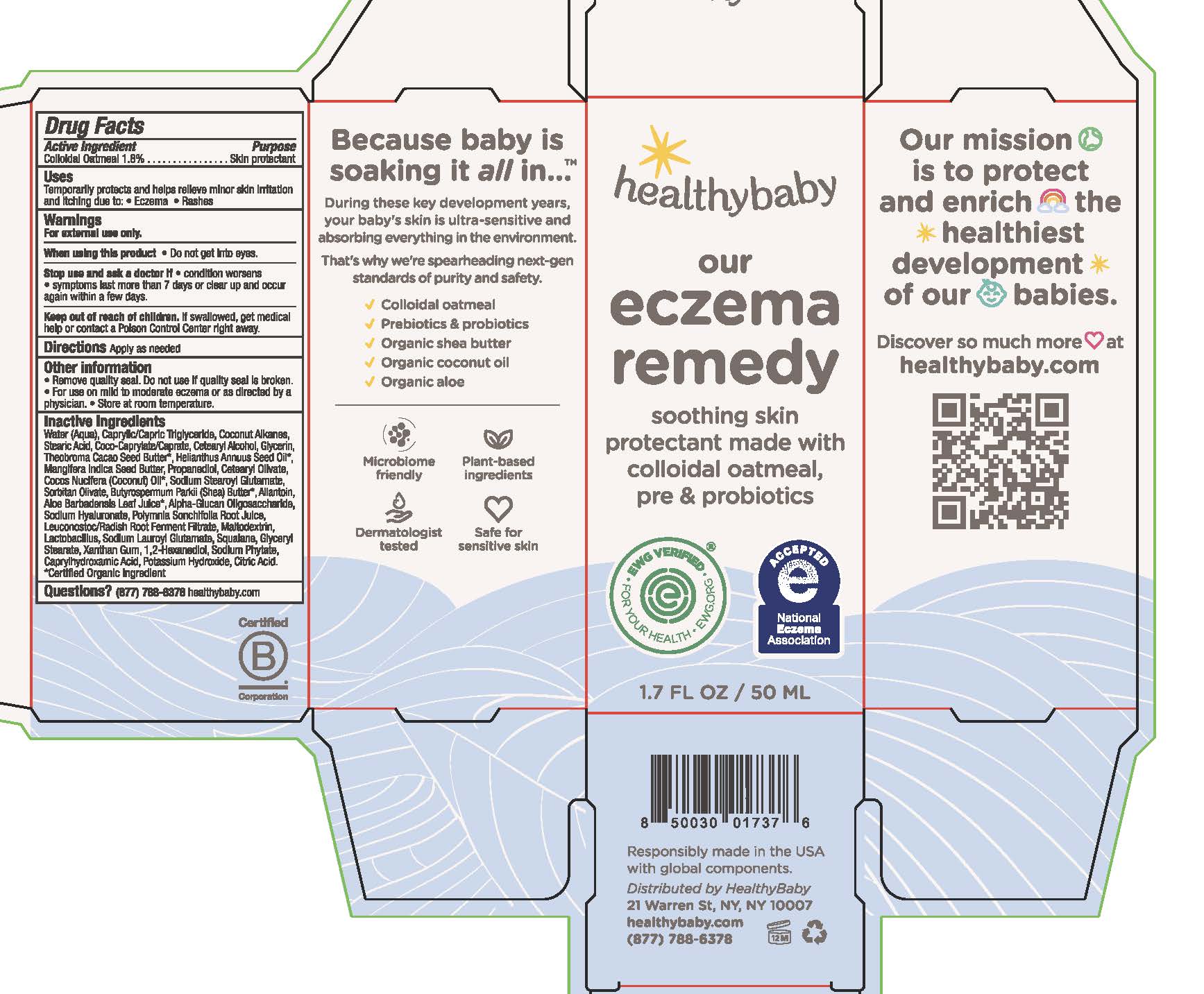 DRUG LABEL: Our Eczema Remedy
NDC: 84073-100 | Form: CREAM
Manufacturer: Fewer Better Things
Category: otc | Type: HUMAN OTC DRUG LABEL
Date: 20250721

ACTIVE INGREDIENTS: OATMEAL 1.8 g/100 g
INACTIVE INGREDIENTS: SODIUM HYALURONATE; COCOS NUCIFERA (COCONUT) OIL; SODIUM STEAROYL GLUTAMATE; SORBITAN OLIVATE; THEOBROMA CACAO (COCOA) SEED BUTTER; SODIUM PHYTATE; ALLANTOIN; CETEARYL ALCOHOL; PROPANEDIOL; COCO-CAPRYLATE/CAPRATE; LACTOBACILLUS; SODIUM LAUROYL GLUTAMATE; XANTHAN GUM; POTASSIUM HYDROXIDE; CAPRYLHYDROXAMIC ACID; COCONUT ALKANES; CETEARYL OLIVATE; BUTYROSPERMUM PARKII (SHEA) BUTTER; GLYCERYL STEARATE; HELIANTHUS ANNUUS (SUNFLOWER) SEED OIL; WATER; CAPRYLIC/CAPRIC TRIGLYCERIDE; STEARIC ACID; ALPHA-GLUCAN OLIGOSACCHARIDE; GLYCERIN; POLYMNIA SONCHIFOLIA ROOT JUICE; LEUCONOSTOC/RADISH ROOT FERMENT FILTRATE; MALTODEXTRIN; CITRIC ACID; MANGIFERA INDICA SEED BUTTER; ALOE BARBADENSIS LEAF JUICE; SQUALANE; 1,2-HEXANEDIOL

Our Eczema Remedy - 84073-100-01

Drug Facts

Active Ingredients

Colloidal Oatmeal 1.8%

Purpose

Skin protectant

Uses

Temporarily protects and helps relieve minor skin irritation and itching due to: • Eczema • Rashes

Warnings

For external use only

When using this product

• Do not get into eyes

Stop use and ask a doctor if

• condition worsens • symptoms last more than 7 days or clear up and occur again within a few days

Keep out of reach of children.

If swallowed, get medical help or contact a Poison Control Center right away

Directions

Apply as needed

Other Information

• Remove quality seal. Do not use if quality seal is broken
• For use on mild to moderate eczema or as directed by a physician
• Store at room temperature

Inactive Ingredients

Water (Aqua), Caprylic/Capric Triglyceride, Coconut Alkanes, Stearic Acid, Coco-Caprylate/Caprate, Cetearyl Alcohol, Glycerin, Theobroma Cacao Seed Butter*, Helianthus Annuus Seed Oil*, Mangifera Indica Seed Butter, Propanediol, Cetearyl Olivate, Cocos Nucifera (Coconut) Oil*, Sodium Stearoyl Glutamate, Sorbitan Olivate, Butyrospermum Parkii (Shea) Butter*, Allantoin, Aloe Barbadensis Leaf Juice*, Alpha-Glucan Oligosaccharide, Sodium Hyaluronate, Polymnia Sonchifolia Root Juice, Leuconostoc/Radish Root Ferment Filtrate, Maltodextrin, Lactobacillus, Sodium Lauroyl Glutamate, Squalane, Glyceryl Stearate, Xanthan Gum, 1,2-Hexanediol, Sodium Phytate, Caprylhydroxamic Acid, Potassium Hydroxide, Citric Acid. *Certified Organic Ingredient

Questions?

(877) 788-6378 healthybaby.com